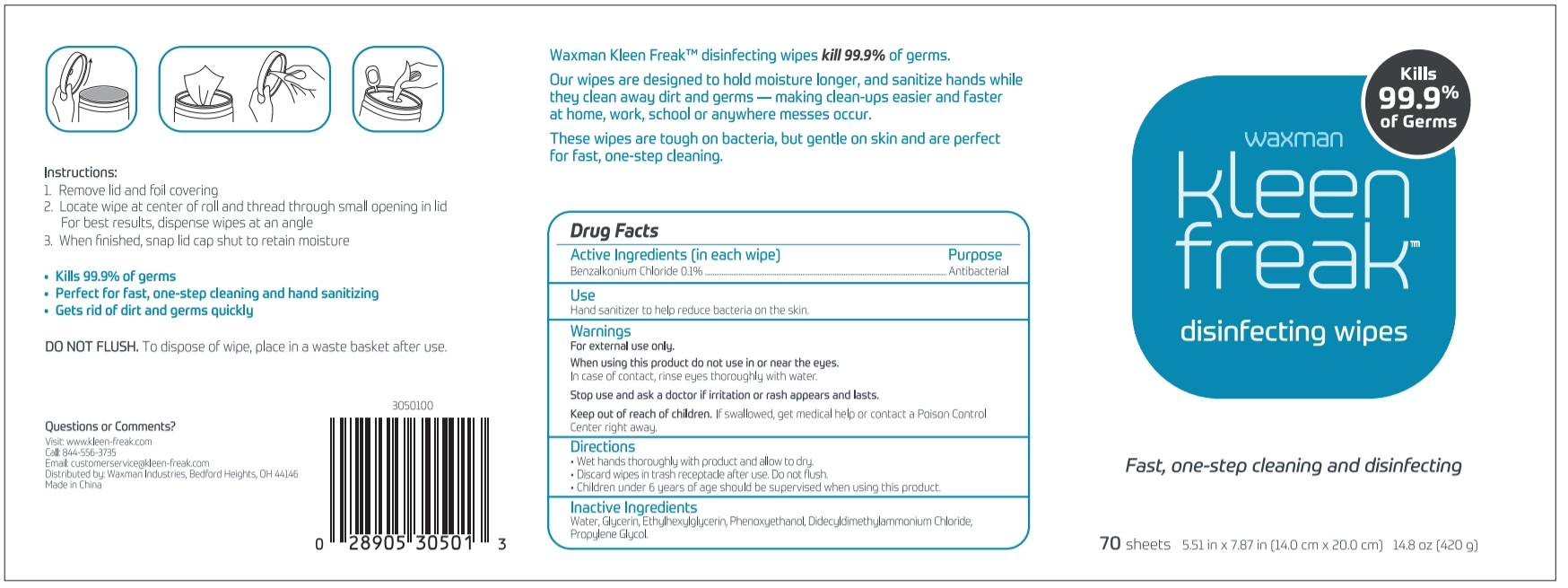 DRUG LABEL: Disinfecting Wipes
NDC: 54237-021 | Form: CLOTH
Manufacturer: Guangzhou Daieme Cosmetic Co,.Ltd
Category: otc | Type: HUMAN OTC DRUG LABEL
Date: 20201013

ACTIVE INGREDIENTS: BENZALKONIUM CHLORIDE 0.28 g/70 1
INACTIVE INGREDIENTS: PHENOXYETHANOL; DIDECYLDIMONIUM CHLORIDE; FRAGRANCE LAVENDER & CHIA F-153480; PROPYLENE GLYCOL; ETHYLHEXYLGLYCERIN; GLYCERIN; WATER

DOSAGE AND ADMINISTRATION

Keep in a cool and dry place and aviod storage in direct sunlight.

INACTIVE INGREDIENT

Glycerin，Propylene Glycol , Didecyldimethylammonium Chloride,Phenoxyethanol, Ethylhexylglycerin, Non-woven Fabric，Water，Fragrance

INDICATIONS AND USAGE

1.Remove lid and foil covering.
2. Locate wipe at center of roll and thread through small opening inlid.For best results, dispense wipes at an angle,Wet hands thoroughly with product and alow to dry.

3. When finished, snap lid cap shut to retain moisture.

ACTIVE INGREDIENT

Benzalkonium Chloride

keep out of reach of children

PURPOSE

Disinfection
Sterilization
No Rinseing

WARNINGS

For external use only.